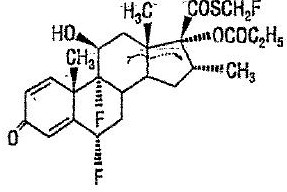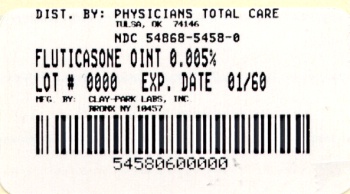 DRUG LABEL: Fluticasone Propionate
NDC: 54868-5458 | Form: OINTMENT
Manufacturer: Physicians Total Care, Inc.
Category: prescription | Type: HUMAN PRESCRIPTION DRUG LABEL
Date: 20100520

ACTIVE INGREDIENTS: FLUTICASONE PROPIONATE 0.05 mg/1 g
INACTIVE INGREDIENTS: MINERAL OIL; PROPYLENE GLYCOL; SORBITAN SESQUIOLEATE

Rx only

For Dermatologic Use Only—Not for Ophthalmic Use.

DESCRIPTION

Fluticasone propionate ointment, 0.005% contains fluticasone propionate [(6α,11β,16α,17α)-6,9,-difluoro-11-hydroxy-16-methyl-3-oxo-17-(1-oxopropoxy)androsta-1,4-diene-17-carbothioic acid, S-fluoromethyl ester], a synthetic fluorinated corticosteroid, for topical dermatologic use. The topical corticosteroids constitute a class of primarily synthetic steroids used as anti-inflammatory and antipruritic agents.

Chemically, fluticasone propionate is C25H31F3O5S. It has the following structural formula:

Fluticasone propionate has a molecular weight of 500.6. It is a white to off-white powder and is insoluble in water.

Each gram of fluticasone propionate ointment, 0.005% contains fluticasone propionate 0.05 mg in a base of liquid paraffin, microcrystalline wax, propylene glycol, and sorbitan sesquioleate.

CLINICAL PHARMACOLOGY

Like other topical corticosteroids, fluticasone propionate has anti-inflammatory, antipruritic, and vasoconstrictive properties. The mechanism of the anti-inflammatory activity of the topical steroids, in general, is unclear. However, corticosteroids are thought to act by the induction of phospholipase A2 inhibitory proteins, collectively called lipocortins. It is postulated that these proteins control the biosynthesis of potent mediators of inflammation such as prostaglandins and leukotrienes by inhibiting the release of their common precursor, arachidonic acid. Arachidonic acid is released from membrane phospholipids by phospholipase A2.

Fluticasone propionate is lipophilic and has a strong affinity for the glucocorticoid receptor. It has weak affinity for the progesterone receptor, and virtually no affinity for the mineralocorticoid, estrogen, or androgen receptors. The therapeutic potency of glucocorticoids is related to the half-life of the glucocorticoid-receptor complex. The half-life of the fluticasone propionate-glucocorticoid receptor complex is approximately 10 hours.

Studies performed with fluticasone propionate ointment, 0.005% indicate that it is in the medium range of potency as compared with other topical corticosteroids.

Pharmacokinetics Absorption

The activity of fluticasone propionate ointment, 0.005% is due to the parent drug, fluticasone propionate. The extent of percutaneous absorption of topical corticosteroids is determined by many factors, including the vehicle and the integrity of the epidermal barrier. Occlusive dressing enhances penetration. Topical corticosteroids can be absorbed from normal intact skin. Inflammation and/or other disease processes in the skin increase percutaneous absorption.

In a study of 6 healthy volunteers applying 25 g of fluticasone propionate ointment 0.005% twice daily to the trunk and legs for up to 5 days under occlusion, plasma levels of fluticasone ranged from 0.08 to 0.22 ng/mL.-

In an animal study using radiolabeled 0.05% fluticasone propionate cream and ointment preparations, rats received a topical dose of 1 g/kg for a 24-hour period. Total recovery of radioactivity was approximately 80% at the end of 7 days. The majority of the dose (73%) was recovered from the surface of the application site. Less than 1% of the dose was recovered in the skin at the application site. Approximately 5% of the dose was absorbed systemically through the skin. Absorption from the skin continued for the duration of the study (7 days), indicating a long retention time at the application site.

Distribution

Following intravenous administration of 1 mg of fluticasone propionate in healthy volunteers, the initial disposition phase for fluticasone propionate was rapid and consistent with its high lipid solubility and tissue binding. The apparent volume of distribution averaged 4.2 L/kg (range, 2.3-16.7 L/kg). The percentage of fluticasone propionate bound to human plasma proteins averaged 91%. Fluticasone propionate is weakly and reversibly bound to erythrocytes. Fluticasone propionate is not significantly bound to human transcortin.

Metabolism

No metabolites of fluticasone propionate were detected in an in vitro study of radiolabeled fluticasone propionate incubated in a human skin homogenate. The total blood clearance of systemically absorbed fluticasone propionate averages 1093 mL/min (range, 618-1702 mL/min) after a 1-mg intravenous dose, with renal clearance accounting for less than 0.02% of the total. Fluticasone propionate is metabolized in the liver by cytochrome P450 3A4-mediated hydrolysis of the 5-fluoromethyl carbothioate grouping. This transformation occurs in 1 metabolic step to produce the inactive 17-β-carboxylic acid metabolite, the only known metabolite detected in man. This metabolite has approximately 2000 times less affinity than the parent drug for the glucocorticoid receptor of human lung cytosol in vitro and negligible pharmacological activity in animal studies. Other metabolites detected in vitro using cultured human hepatoma cells have not been detected in man.

Excretion

Following an intravenous dose of 1 mg in healthy volunteers, fluticasone propionate showed polyexponential kinetics and had an average terminal half-life of 7.2 hours (range, 3.2-11.2 hours).

INDICATIONS AND USAGE

Fluticasone propionate ointment, 0.005% is a medium potency corticosteroid indicated for the relief of the inflammatory and pruritic manifestations of corticosteroid-responsive dermatoses in adult patients.

CONTRAINDICATIONS

Fluticasone propionate ointment, 0.005% is contraindicated in those patients with a history of hypersensitivity to any of the components in the preparation.

PRECAUTIONS

Enter section text here

ADVERSE REACTIONS

In controlled clinical trials, the total incidence of adverse reactions associated with the use of fluticasone propionate ointment, 0.005% was approximately 4%. These adverse reactions were usually mild, self-limiting, and consisted primarily of pruritus, burning, hypertrichosis, increased erythema, hives, irritation, and lightheadedness. Each of these events occurred individually in less than 1% of patients. In a study of 35 pediatric patients treated with fluticasone propionate ointment 0.005% for atopic dermatitis over at least 35% of body surface area, subnormal adrenal function was observed with cosyntropin stimulation testing at the end of 3 to 4 weeks of treatment in 4 patients who had normal testing prior to treatment. It is not known if these patients had recovery of adrenal function because follow-up testing was not performed (see PRECAUTIONS:Pediatric Use, and ADVERSE REACTIONS). Telangiectasia on the face was noted in one patient on the eighth day of a four week treatment period. Facial use was discontinued and the telangiectasia resolved.

The following additional local adverse reactions have been reported infrequently with topical corticosteroids, including fluticasone propionate, and they may occur more frequently with the use of occlusive dressings and higher potency corticosteroids. These reactions are listed in an approximately decreasing order of occurrence: dryness, folliculitis, acneiform eruptions, hypopigmentation, perioral dermatitis, allergic contact dermatitis, secondary infection, skin atrophy, striae, and miliaria. Also, there are discontinuation of potent topical corticosteroid products.

OVERDOSAGE

Topically applied fluticasone propionate ointment, 0.005% can be absorbed in sufficient amounts to produce systemic effects (see PRECAUTIONS).

DOSAGE AND ADMINISTRATION

Apply a thin film of fluticasone propionate ointment, 0.005% to the affected skin areas twice daily. Rub in gently.

Fluticasone propionate ointment, 0.005% should not be used with occlusive dressings.

Geriatric Use

In studies where geriatric patients (65 years of age or older, see PRECAUTIONS) have been treated with fluticasone propionate ointment, 0.005%, safety did not differ from that in younger patients; therefore, no dosage adjustment is recommended.

HOW SUPPLIED

Fluticasone Propionate Ointment, 0.005% is available as follows:

30 g tube (NDC 54868-5458-1)

60 g tube (NDC 54868-5458-0)

STORAGE

Store at 20-25°C (68-77°F) [see USP Controlled Room Temperature].

DISTRIBUTED BY PERRIGO®

ALLEGAN, MI 49010

Manufactured by:

Perrigo

Bronx, NY 10457

Rev. 07/09

0A300 RC J4

Additional barcode labeling by:
Physicians Total Care, Inc.
Tulsa, OK 74146

PRINCIPAL DISPLAY PANEL

Fluticasone Propionate Ointment, 0.005%